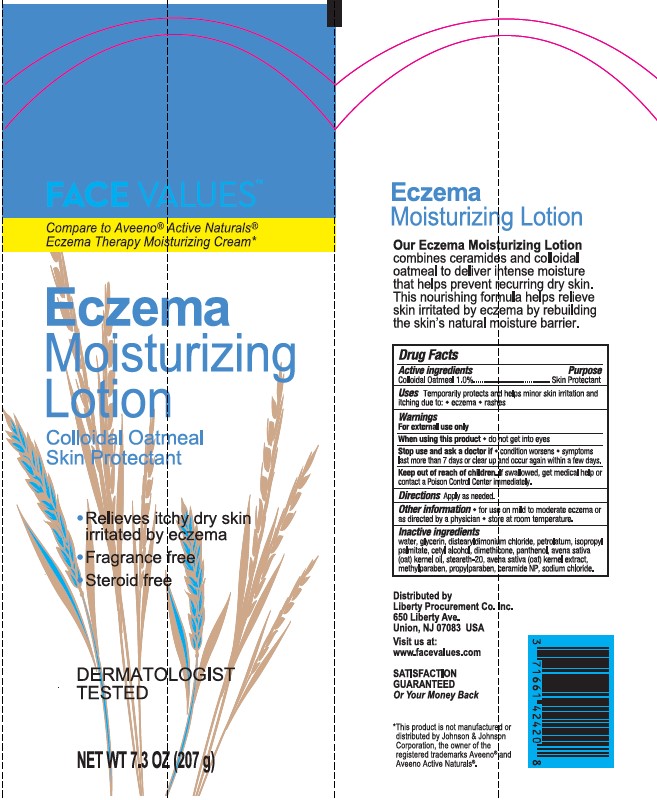 DRUG LABEL: ECZEMA MOISTURIZING
NDC: 63940-050 | Form: LOTION
Manufacturer: Harmon Stores Inc.
Category: otc | Type: HUMAN OTC DRUG LABEL
Date: 20241021

ACTIVE INGREDIENTS: OATMEAL 10 mg/1 g
INACTIVE INGREDIENTS: WATER; GLYCERIN; DISTEARYLDIMONIUM CHLORIDE; PETROLATUM; ISOPROPYL PALMITATE; CETYL ALCOHOL; DIMETHICONE; PANTHENOL; OAT KERNEL OIL; STEARETH-20; OAT; METHYLPARABEN; PROPYLPARABEN; CERAMIDE NP; SODIUM CHLORIDE

FACE VALUES EXZEMA MOISTURIZING LOTION

Active Ingredients

Colloidal Oatmeal 1.0%

Purpose

Skin Protectant

Uses

Temporarily protects and helps minor skin irritation and itching due to: • eczema • rashes

Warnings

For external use only

When using this product

• do not get into eyes

Stop use and ask a doctor if

• condition worsens • symptoms last more than 7 days or clear up and occur again within a few days.

Keep out of reach of children.

If swallowed, get medical help or contact a Poison Control Center immediately.

Directions

Apply as needed.

Other information

- for use on mild to moderate eczema or as directed by a physician
- store at room temperature.

Inactive Ingredients

water, glycerin, distearyldimonium chloride, petrolatum, isopropyl palmitate, cetyl alcohol, dimethicone, panthenol, avena sativa (oat) kernel oil, steareth-20, avena sativa (oat) kernel extract, methylparaben, propylparaben, ceramide NP, sodium chloride.